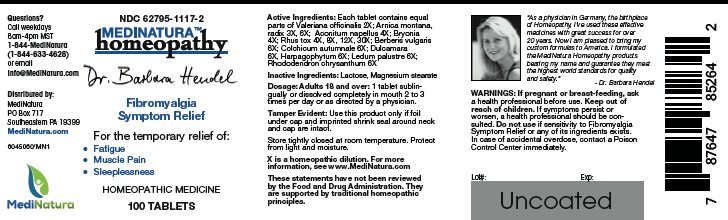 DRUG LABEL: Hendel Fibromyalgia Symptom Relief
NDC: 62795-1117 | Form: TABLET
Manufacturer: MediNatura Inc
Category: homeopathic | Type: HUMAN OTC DRUG LABEL
Date: 20180417

ACTIVE INGREDIENTS: VALERIAN 2 [hp_X]/1 1; ARNICA MONTANA ROOT 3 [hp_X]/1 1; ACONITUM NAPELLUS 4 [hp_X]/1 1; BRYONIA ALBA ROOT 4 [hp_X]/1 1; TOXICODENDRON PUBESCENS LEAF 4 [hp_X]/1 1; BERBERIS VULGARIS ROOT BARK 6 1/1 1; COLCHICUM AUTUMNALE BULB 6 [hp_X]/1 1; SOLANUM DULCAMARA TOP 6 [hp_X]/1 1; HARPAGOPHYTUM PROCUMBENS WHOLE 6 [hp_X]/1 1; RHODODENDRON TOMENTOSUM LEAFY TWIG 6 [hp_X]/1 1; RHODODENDRON AUREUM LEAF 6 [hp_X]/1 1
INACTIVE INGREDIENTS: LACTOSE MONOHYDRATE; MAGNESIUM STEARATE

Hendel Fibromyalgia Symptom Relief

WARNINGS

If pregnant or breast-feeding, ask a health professional before use. Keep out of reach of children. If symptoms persist or worsen, a health professional should be consulted. Do not use if sensitivity to Fibromyalgia Symptom Relief or any of its ingredients exists. In case of accidental overdose, contact a Poison Control Center immediately.

KEEP OUT OF REACH OF CHILDREN

INDICATIONS

Fibromyalgia Symptom Relief

INGREDIENTS

Each tablet contains equal parts of Valeriana officinalis 2X; Arnica montana,radix 3X, 6X; Aconitum napellus 4X; Bryonia4X; Rhus tox 4X, 8X, 12X, 30X; Berberis vulgaris 6X; Colchicum autumnale 6X; Dulcamara6X, Harpagophytum 6X; Ledum palustre 6X; Rhododendron chrysanthum 6X

INACTIVE INGREDIENT

Lactose, Magnesium stearate

DIRECTIONS

Adults 18 and over: 1 tablet sublingually or dissolved completely in mouth 2 to 3 times per day or as directed by a physician

USES

For the temporary relief of:

• Fatigue
• Muscle Pain
• Sleeplessness